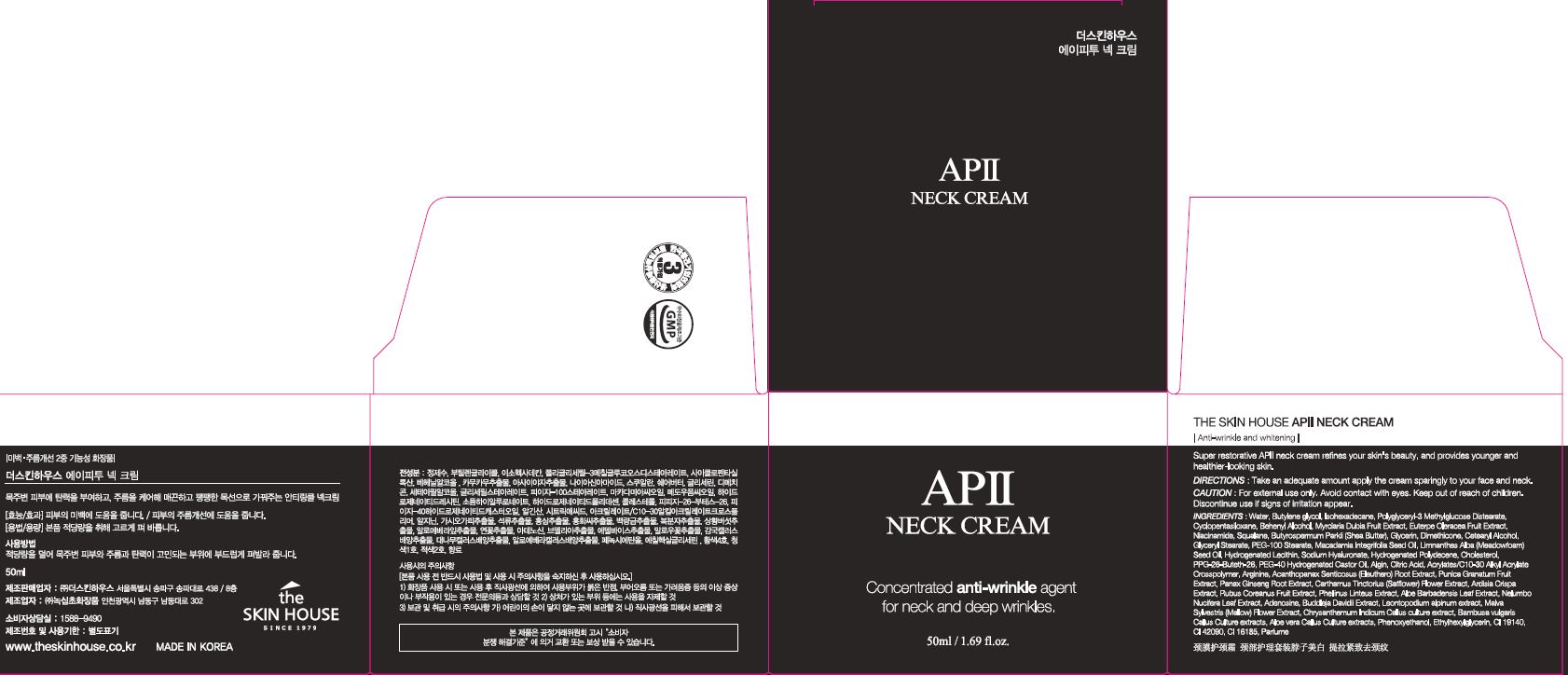 DRUG LABEL: AP II NeckCream
NDC: 73590-0053 | Form: CREAM
Manufacturer: NOKSIBCHO cosmetic Co., Ltd.
Category: otc | Type: HUMAN OTC DRUG LABEL
Date: 20200907

ACTIVE INGREDIENTS: ADENOSINE 0.04 g/100 mL; NIACINAMIDE 2 g/100 mL
INACTIVE INGREDIENTS: WATER

Drug Facts

ACTIVE INGREDIENT

adenosine, niacinamide

INACTIVE INGREDIENT

Water
Butylene glycol
Isohexadecane
Polyglyceryl-3 Methylglucose Distearate
Cyclopentasiloxane
Behenyl Alcohol
Myrciaria Dubia Fruit Extract
Euterpe Oleracea Fruit Extract
Squalane
Butyrospermum Parkii (Shea Butter)
Glycerin
Dimethicone
Cetearyl Alcohol
Glyceryl Stearate
PEG-100 Stearate
Macadamia Integrifolia Seed Oil
Limnanthes Alba (Meadowfoam) Seed Oil
Hydrogenated Lecithin
Sodium Hyaluronate
Hydrogenated Polydecene
Cholesterol
PPG-26-Buteth-26
PEG-40 Hydrogenated Castor Oil
Algin
Citric Acid
Acrylates/C10-30 Alkyl Acrylate Crosspolymer
Arginine
Acanthopanax Senticosus (Eleuthero) Root Extract
Punica Granatum Fruit Extract
Panax Ginseng Root Extract
Carthamus Tinctorius (Safflower) Flower Extract
Ardisia Crispa Extract
Rubus Coreanus Fruit Extract
Phellinus Linteus Extract
Aloe Barbadensis Leaf Extract
Nelumbo Nucifera Leaf Extract
CI 19140
CI 42090
CI 16185
Buddleja Davidii Extract
Leontopodium alpinum extract
Malva Sylvestris (Mallow) Flower Extract
Chrysanthemum Indicum Callus culture extract
Bambusa vulgaris Callus Culture extracts
Aloe vera Callus Culture extracts
Phenoxyethanol
Ethylhexylglycerin
Perfume

PURPOSE

anti-wrinkle

keep out of reach of the children

INDICATIONS AND USAGE

apply proper amount to the skin

WARNINGS

For external use only
When using this product

■ if the following symptoms occurs after use, stop use and consult with a skin specialist

red specks, swelling, itching

■ don’t use on the part where there is injury, eczema, or dermatitis

Keep out of reach of children

■ if swallowed, get medical help or contact a person control center immediately